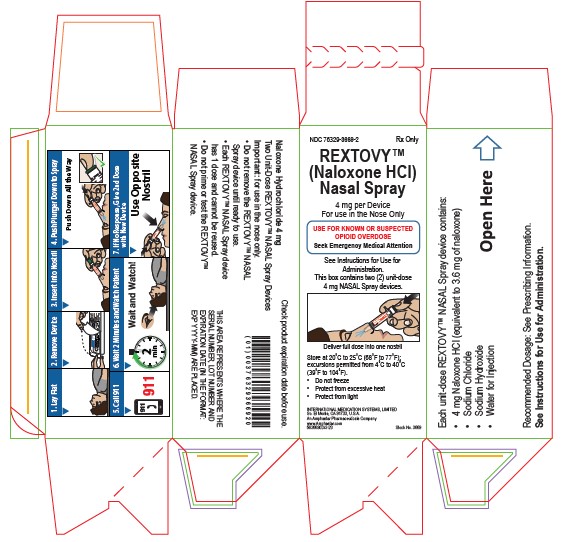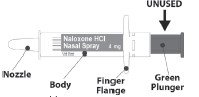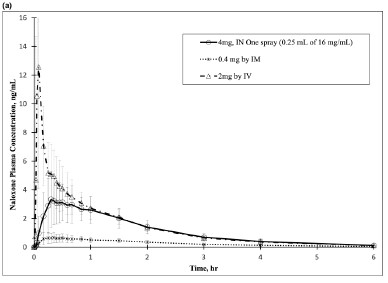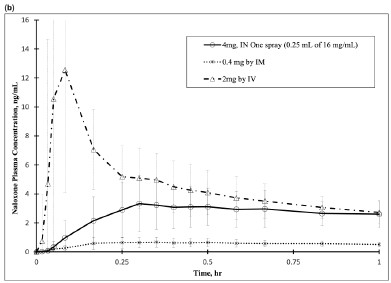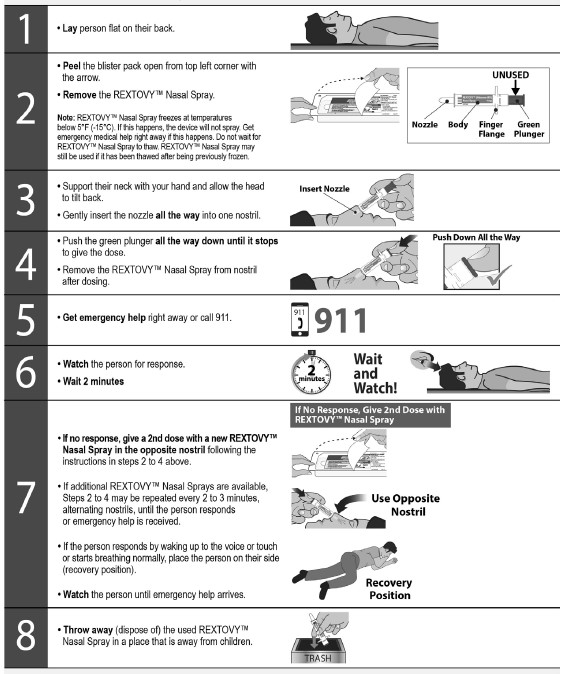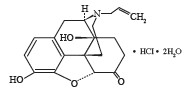 DRUG LABEL: REXTOVY
NDC: 76329-3669 | Form: SPRAY
Manufacturer: International Medication Systems, Ltd.
Category: prescription | Type: HUMAN PRESCRIPTION DRUG LABEL
Date: 20240515

ACTIVE INGREDIENTS: NALOXONE HYDROCHLORIDE 4 mg/0.25 mL
INACTIVE INGREDIENTS: SODIUM CHLORIDE; SODIUM HYDROXIDE; WATER

HIGHLIGHTS OF PRESCRIBING INFORMATION

These highlights do not include all the information needed to use REXTOVY™ Nasal Spray safely and effectively. See full prescribing information for REXTOVY™ Nasal Spray.
REXTOVY™ (naloxone hydrochloride) Nasal Spray
Initial U.S. Approval: 1971

1 INDICATIONS AND USAGE

REXTOVY Nasal Spray is an opioid antagonist indicated for the emergency treatment of known or suspected opioid overdose, as manifested by respiratory and/or central nervous system depression for adults and pediatric patients. (1)
REXTOVY Nasal Spray is intended for immediate administration as emergency therapy in settings where opioids may be present. (1)
REXTOVY Nasal Spray is not a substitute for emergency medical care. (1)

2 DOSAGE AND ADMINISTRATION

- REXTOVY Nasal Spray is for intranasal use only. (2.1)
- Seek emergency medical care immediately after use. (2.1)
- Administer one spray of REXTOVY Nasal Spray to adults or pediatric patients intranasally into one nostril. (2.2)
- Administer additional doses of REXTOVY Nasal Spray using a new nasal spray device with each dose if the patient does not respond or responds and then relapses into respiratory depression. Additional doses of REXTOVY Nasal Spray may be given every 2 to 3 minutes until emergency medical assistance arrives. (2.2)
- Additional supportive and/or resuscitative measures may be helpful while awaiting emergency medical assistance. (2.2)

3 DOSAGE FORMS AND STRENGTHS

Nasal Spray: 4 mg of naloxone hydrochloride per device. Each unit-dose REXTOVY nasal spray device delivers a single spray containing 4 mg of naloxone hydrochloride

4 CONTRAINDICATIONS

Hypersensitivity to naloxone hydrochloride or to any of the other ingredients.

5 WARNINGS AND PRECAUTIONS

- Risk of Recurrent Respiratory and CNS Depression: Due to the duration of action of naloxone relative to the opioid, keep patient under continued surveillance and administer repeat doses of naloxone using a new nasal spray device with each dose, as necessary, while awaiting emergency medical assistance. (5.1)
- Risk of Limited Efficacy with Partial Agonists or Mixed Agonists/Antagonists: Reversal of respiratory depression caused by partial agonists or mixed agonists/antagonists, such as buprenorphine and pentazocine, may be incomplete. Larger or repeat doses may be required. (5.2)
- Precipitation of Severe Opioid Withdrawal: Use in patients who are opioid dependent may precipitate opioid withdrawal. In neonates, opioid withdrawal may be life-threatening if not recognized and properly treated. Monitor for the development of opioid withdrawal. (5.3)
- Risk of Cardiovascular (CV) Effects: Abrupt postoperative reversal of opioid depression may result in adverse CV effects. These events have primarily occurred in patients who had preexisting CV disorders or received other drugs that may have similar adverse CV effects. Monitor these patients closely in an appropriate healthcare setting after use of REXTOVY Nasal Spray. (5.3)

6 ADVERSE REACTIONS

The following adverse reactions were observed in a REXTOVY Nasal Spray clinical study: oral paraesthesia (3.7%), headache (3.7%) (6)

To report SUSPECTED ADVERSE REACTIONS, contact Amphastar Pharmaceuticals, Inc. at 1-800-423-4136 or FDA at 1-800-FDA-1088 or www.fda.gov/medwatch.

FULL PRESCRIBING INFORMATION

1 INDICATIONS AND USAGE

REXTOVY Nasal Spray is indicated for emergency treatment of known or suspected opioid overdose, as manifested by respiratory and/or central nervous system depression, for adult and pediatric patients.

REXTOVY Nasal Spray is intended for immediate administration as emergency therapy in settings where opioids may be present.

REXTOVY Nasal Spray is not a substitute for emergency medical care.

2 DOSAGE AND ADMINISTRATION

2.1 Important Administration Instructions

- REXTOVY Nasal Spray is for intranasal use only.
- The device is ready to use. Do not prime or test prior to administration.
- Do not attempt to reuse REXTOVY Nasal Spray. Each unit-dose device contains a single dose of naloxone and cannot be reused.

Figure 1 REXTOVY Nasal Spray Device

- Because treatment of suspected opioid overdose must be performed by someone other than the patient, instruct the prescription recipient to inform those around them about the presence of REXTOVY Nasal Spray and the Instructions for Use.
- Instruct the users or caregiver to read the Instructions for Use at the time they receive a prescription for REXTOVY Nasal Spray. Emphasize the following instructions to the patient or caregiver:
- Administer REXTOVY Nasal Spray as quickly as possible because prolonged respiratory depression may result in damage to the central nervous system or death.
- Always seek immediate emergency medical assistance after the first dose of REXTOVY Nasal Spray has been administered in the event of a suspected, potentially life-threatening opioid emergency because the duration of action of most opioids exceeds that of naloxone hydrochloride. Keep the patient under continued surveillance and administer repeated doses of REXTOVY Nasal Spray, as necessary, until emergency personnel arrive [see Warnings and Precautions (5.1)].
- Administer REXTOVY Nasal Spray according to the printed instructions on the carton and the Instructions for Use.

◦ Place the patient in the supine position. Prior to administration, be sure the device nozzle is inserted in either nostril of the patient and provide support to the back of the neck to allow the head to tilt back. Do not prime or test the device prior to administration.

◦To administer the dose, press firmly on the green plunger of the device and remove the REXTOVY Nasal Spray nozzle from the nostril after use.
◦If the patient responds by waking up to the voice or touch or starts breathing normally, place the person on their side (recovery position) as shown in the Instructions for Use and call for emergency medical assistance immediately after the first dose of REXTOVY Nasal Spray.

◦Administer additional doses of REXTOVY Nasal Spray, using a new REXTOVY Nasal Spray, every 2 to 3 minutes as needed if the patient does not respond or responds and then relapses into respiratory depression. Administer REXTOVY Nasal Spray in alternate nostrils with each dose [see Dosing and Administration (2.2)].

2.2 Dosing in Adults and Pediatric Patients

Initial Dosing
The recommended initial dose of REXTOVY Nasal Spray in adults and pediatric patients is one spray delivered by intranasal administration, which delivers 4 mg of naloxone hydrochloride.

Repeat Dosing
Seek emergency medical assistance as soon as possible after administering the REXTOVY Nasal Spray. The requirement for repeat doses of REXTOVY Nasal Spray depends upon the amount, type, and route of administration of the opioid being antagonized.

Administer REXTOVY Nasal Spray in alternate nostrils with each dose.

If the patient responds to REXTOVY Nasal Spray and relapses back into respiratory depression before emergency assistance arrives, administer an additional dose of REXTOVY Nasal Spray in opposite nostril using a new REXTOVY Nasal Spray device and continue surveillance of the patient.

If the desired response is not obtained after 2 minutes, administer an additional dose of REXTOVY Nasal Spray using a new REXTOVY Nasal Spray device. If there is still no response and additional doses are available, administer additional doses of REXTOVY Nasal Spray every 2 to 3 minutes using a new REXTOVY Nasal Spray device with each dose until emergency medical assistance arrives.

Additional supportive and/or resuscitative measures may be helpful while awaiting emergency medical assistance.

2.3 Dosing Modifications due to Partial Agonists or Mixed Agonist/Antagonists

Reversal of respiratory depression by partial agonists or mixed agonist/antagonists, such as buprenorphine and pentazocine, may be incomplete and require higher doses of naloxone hydrochloride or repeated administration of REXTOVY Nasal Spray using a new REXTOVY Nasal Spray [see Warnings and Precautions (5.2)].

3 DOSAGE FORMS AND STRENGTHS

Nasal spray: 4 mg of naloxone hydrochloride per device. Each unit-dose REXTOVY nasal spray device delivers a single spray containing 4 mg of naloxone hydrochloride.

4 CONTRAINDICATIONS

REXTOVY Nasal Spray is contraindicated in patients known to be hypersensitive to naloxone hydrochloride or to any of the other ingredients.

5 WARNINGS AND PRECAUTIONS

5.1 Risk of Recurrent Respiratory and Central Nervous System Depression

The duration of action of most opioids may exceed that of REXTOVY Nasal Spray resulting in a return of respiratory and/or central nervous system depression after an initial improvement in symptoms. Therefore, it is necessary to seek emergency medical assistance immediately after administration of REXTOVY Nasal Spray and to keep the patient under continued surveillance. Administer additional doses of REXTOVY Nasal Spray if the patient is not adequately responding or responds and then relapses back into respiratory depression, as necessary [see Dosage and Administration (2.2)]. Additional supportive and/or resuscitative measures may be helpful while awaiting emergency medical assistance.

5.2 Risk of Limited Efficacy with Partial Agonists or Mixed Agonist/Antagonists

Reversal of respiratory depression by partial agonists or mixed agonist/antagonists such as buprenorphine and pentazocine, may be incomplete. Larger or repeat doses of naloxone hydrochloride may be required to antagonize buprenorphine because the latter has a long duration of action due to its slow rate of binding and subsequent slow dissociation from the opioid receptor [see Dosage and Administration (2.3)]. Buprenorphine antagonism is characterized by a gradual onset of the reversal effects and a decreased duration of action of the normally prolonged respiratory depression.

5.3 Precipitation of Severe Opioid Withdrawal

The use of REXTOVY Nasal Spray in patients who are opioid dependent may precipitate opioid withdrawal characterized by the following signs and symptoms: body aches, diarrhea, tachycardia, fever, runny nose, sneezing, piloerection, sweating, yawning, nausea or vomiting, nervousness, restlessness or irritability, shivering or trembling, abdominal cramps, weakness, and increased blood pressure. In neonates, opioid withdrawal may be life-threatening if not recognized and properly treated and may include the following signs and symptoms: convulsions, excessive crying, and hyperactive reflexes. Monitor the patient for the development of the signs and symptoms of opioid withdrawal.

Abrupt postoperative reversal of opioid depression after using naloxone hydrochloride may result in nausea, vomiting, sweating, tremulousness, tachycardia, hypotension, hypertension, seizures, ventricular tachycardia and fibrillation, pulmonary edema, and cardiac arrest. Death, coma, and encephalopathy have been reported as sequelae of these events. These events have primarily occurred in patients who had pre-existing cardiovascular disorders or received other drugs that may have similar adverse cardiovascular effects. After use of naloxone hydrochloride, monitor patients with pre-existing cardiac disease or patients who have received medications with potential adverse cardiovascular effects for hypotension, ventricular tachycardia or fibrillation, and pulmonary edema in an appropriate healthcare setting. It has been suggested that the pathogenesis of pulmonary edema associated with the use of naloxone hydrochloride is similar to neurogenic pulmonary edema, i.e., a centrally mediated massive catecholamine response leading to a dramatic shift of blood volume into the pulmonary vascular bed resulting in increased hydrostatic pressures.

There may be clinical settings, particularly the postpartum period in neonates with known or suspected exposure to maternal opioid use, where it is preferable to avoid the abrupt precipitation of opioid withdrawal symptoms. In these settings, consider use of an alternative, naloxone-containing product that can be titrated to effect and, where applicable, dosed according to weight [see Use in Specific Populations (8.4)].

6 ADVERSE REACTIONS

The following serious adverse reactions are discussed elsewhere in the labeling:

- Recurrent Respiratory and Central Nervous System Depression [see Warnings and Precautions (5.1)]
- Precipitation of Severe Opioid Withdrawal [see Warnings and Precautions (5.3)]

6.1 Clinical Trials Experience

Because clinical studies are conducted under widely varying conditions, adverse reaction rates observed in the clinical studies of a drug cannot be directly compared to the rates in the clinical studies of another drug and may not reflect the rates observed in practice.

In two clinical studies, N002-CL-A3 (Study A3) and N002-CL-A4 (Study A4), which comprised a total of 141 study treatments from 60 subjects, including 55 treatments using 4 mg and 10 mg of REXTOVY nasal spray (IN), the following adverse reactions were observed: oral paraesthesia (3.7%), headache (3.7%).

The following adverse reactions have been observed with other naloxone products: increased blood pressure, constipation, toothache, muscle spasms, musculoskeletal pain, headache, nasal dryness, nasal edema, nasal congestion, nasal inflammation, rhinalgia, xeroderma, abdominal pain, asthenia, dizziness, nasal discomfort, and presyncope.

6.2 Postmarketing Experience

The following adverse events have been identified during the post-approval use of naloxone hydrochloride injection in the postoperative setting. Because these reactions are reported voluntarily from a population of uncertain size, it is not always possible to reliably estimate their frequency or establish a causal relationship to drug exposure: hypotension, hypertension, ventricular tachycardia and fibrillation, dyspnea, pulmonary edema, and cardiac arrest. Death, coma, and encephalopathy have been reported as sequelae of these events. Excessive doses of naloxone hydrochloride in postoperative patients have resulted in significant reversal of analgesia and have caused agitation.

Abrupt reversal of opioid effects in persons who were physically dependent on opioids has precipitated an acute withdrawal syndrome. Signs and symptoms have included: body aches, fever, sweating, runny nose, sneezing, piloerection, yawning, weakness, shivering or trembling, nervousness, restlessness or irritability, diarrhea, nausea or vomiting, abdominal cramps, increased blood pressure, tachycardia. In some patients, there was aggressive behavior upon abrupt reversal of an opioid overdose. In the neonate, opioid withdrawal signs and symptoms also included convulsions, excessive crying, and hyperactive reflexes [see Warnings and Precautions (5.3)].

The following most frequently reported events (in decreasing frequency) have been identified primarily during postapproval use of naloxone hydrochloride (all routes of administration): withdrawal syndrome, vomiting, nonresponsiveness to stimuli, drug ineffective, agitation, somnolence, and loss of consciousness.

8 USE IN SPECIFIC POPULATIONS

8.1 Pregnancy

Risk Summary
Life-sustaining therapy for opioid overdose should not be withheld (see Clinical Considerations). There is an absence of data on naloxone hydrochloride administered for known or suspected opioid overdose in pregnant patients. Available data from retrospective cohort studies on oral naloxone use in pregnant women for opioid use disorder have not identified a drug-associated risk of major birth defects, miscarriage, or other adverse maternal or fetal outcomes. In animal reproduction studies, no embryotoxic or teratogenic effects were observed in mice and rats treated with naloxone hydrochloride during the period of organogenesis at doses equivalent to 6-times and 12-times, respectively, a human dose of 8 mg/day (two REXTOVY Nasal Sprays) based on body surface area comparison (see Data).

The estimated background risk of major birth defects and miscarriage for the indicated population is unknown. In the U.S. general population, the estimated background risk of major birth defects and miscarriage in clinically recognized pregnancies is 2% to 4% and 15% to 20%, respectively.

Clinical Considerations
Disease-associated maternal and/or embryo/fetal risk
An opioid overdose is a medical emergency and can be fatal for the pregnant woman and fetus if left untreated. Treatment with REXTOVY Nasal Spray for opioid overdose should not be withheld because of potential concerns regarding the effects of REXTOVY Nasal Spray on the fetus.

Data
Animal Data
Naloxone hydrochloride was administered during organogenesis to mice and rats at doses 6-times and 12-times, respectively, a human dose of 8 mg (two REXTOVY Nasal Sprays) based on body surface area comparison. These studies demonstrated no embryotoxic or teratogenic effects due to naloxone hydrochloride.

8.2 Lactation

Risk Summary
Naloxone hydrochloride is minimally orally bioavailable and is unlikely to affect the breastfed infant. There is no information regarding the presence of naloxone in human milk, or the effects of naloxone on the breastfed infant or on milk production. Published studies in lactating mothers have shown that naloxone does not affect prolactin or oxytocin hormone levels.

8.4 Pediatric Use

The safety and effectiveness of REXTOVY Nasal Spray have been established in pediatric patients for known or suspected opioid overdose, as manifested by respiratory and/or central nervous system depression. Use of naloxone hydrochloride in all pediatric patients is supported by adult bioequivalence studies coupled with evidence from the safe and effective use of other naloxone hydrochloride drug products. No pediatric studies were conducted for REXTOVY Nasal Spray.

Absorption of naloxone hydrochloride following intranasal administration in pediatric patients may be erratic or delayed. Even when the opiate-intoxicated pediatric patient responds appropriately to naloxone hydrochloride, he/she must be carefully monitored for at least 24 hours, as a relapse may occur as naloxone hydrochloride is metabolized.

In opioid-dependent pediatric patients, (including neonates), administration of naloxone hydrochloride may result in an abrupt and complete reversal of opioid effects, precipitating an acute opioid withdrawal syndrome. There may be clinical settings, particularly the postpartum period in neonates with known or suspected exposure to maternal opioid use, where it is preferable to avoid the abrupt precipitation of opioid withdrawal symptoms. Unlike acute opioid withdrawal in adults, acute opioid withdrawal in neonates manifesting in seizures may be life-threatening if not recognized and properly treated. Other signs and symptoms in neonates may include excessive crying and hyperactive reflexes. In these settings where it may be preferable to avoid the abrupt precipitation of acute opioid withdrawal symptoms, consider use of an alternative, naloxone hydrochloride product that can be dosed according to weight and titrated to effect [see Warnings and Precautions (5.3)].

Also, in situations where the primary concern is for infants at risk for opioid overdose, consider whether the availability of alternate naloxone-containing products may be better suited than REXTOVY Nasal Spray.

8.5 Geriatric Use

Clinical studies of REXTOVY Nasal Spray did not include sufficient numbers of subjects aged 65 and over to determine whether they respond differently from younger subjects. Other reported clinical experience has not identified differences in responses between the elderly and younger patients. Geriatric patients have a greater frequency of decreased hepatic, renal, or cardiac function and of concomitant disease or other drug therapy. Therefore, the systemic exposure of naloxone hydrochloride can be higher in these patients.

11 DESCRIPTION

Naloxone hydrochloride is an opioid antagonist. It is chemically identified as 17-allyl-4,5α-epoxy-3,14-dihydroxymorphinan-6-one hydrochloride dihydrate. Its molecular formula is C19H21NO4 • HCl • 2H2O and has a molecular weight of 399.87 g/mol. It has the following structural formula:

Naloxone hydrochloride dihydrate occurs as a white to slightly off-white powder. It is soluble in water, in dilute acids, and in strong alkali; slightly soluble in alcohol; practically insoluble in ether and in chloroform.

REXTOVY Nasal Spray is a prefilled unit-dose intranasal spray. Naloxone hydrochloride is contained as a solution in a stoppered glass vial within the nasal spray device. Each REXTOVY device delivers a single spray containing 4 mg of naloxone hydrochloride (equivalent to 3.6 mg of naloxone) in 0.25 mL of aqueous solution with a pH of 3.5 to 5.0.

Inactive ingredients include sodium chloride, sodium hydroxide to adjust pH, and water for injection USP.

12 CLINICAL PHARMACOLOGY

12.1 Mechanism of Action

Naloxone hydrochloride is an opioid antagonist that antagonizes opioid effects by competing for the same receptor sites.

Naloxone hydrochloride reverses the effects of opioids, including respiratory depression, sedation, and hypotension. It can also reverse the psychotomimetic and dysphoric effects of agonist-antagonists such as pentazocine.

12.2 Pharmacodynamics

When naloxone hydrochloride is administered intravenously, the onset of action is generally apparent within two minutes. The time to onset of action is shorter for intravenous compared to subcutaneous or intramuscular routes of administration. The duration of action is dependent upon the dose and route of administration of naloxone hydrochloride.

12.3 Pharmacokinetics

In a pharmacokinetic study on healthy adult subjects, the relative bioavailability (BA) of one nasal spray in one nostril (4 mg total dose, 0.25 mL of 16 mg/mL naloxone hydrochloride solution) was compared to a single dose of 0.4 mg naloxone hydrochloride intramuscular (IM) injection, and 2 mg naloxone hydrochloride intravenous (IV) infusion.

Absorption
The pharmacokinetics parameters obtained in the study are shown in Table 1. The pharmacokinetic curves (0-6 hours and 0-30 minutes, respectively) for REXTOVY Nasal Spray 4 mg by IN and naloxone HCl 0.4 mg delivered by IM and 2 mg naloxone by IV are provided in Figure 2, respectively.

Table 1. Mean Pharmacokinetic Parameters for Naloxone Following REXTOVY Nasal Spray, IM Injection and IV Infusion of Naloxone HCl in Healthy Subjects
Parameters | 4 mg REXTOVY; Nasal Spray | 0.4 mg Naloxone HCl; Intramuscular Injection | 2 mg Naloxone HCl; Intravenous Infusion
Population | N=25 | N=27 | N=26
AUC0-6h (ng*hr/mL) | 6.41 ± 1.33 | 1.54 ± 1.27 | 8.44 ± 1.34
AUC0-inf (ng*hr/mL) | 6.63 ± 1.32 | 1.60 ± 1.27 | 8.64 ± 1.33
Cmax (ng/mL) | 3.71 ± 1.55 | 0.73 ± 1.56 | 11.10 ± 2.15
tmax (min) | 32.1 ± 1.6 | 24.4 ± 2.4 | 4.9 ± 1.4
t½ (min) | 67.6 ± 1.2 | 75.7 ± 1.2 | 66.2 ± 1.2
Dose-Normalized Relative; BA (%) vs. IV | 40.7 ± 17.8 | 95.9 ± 28.5 | ---

Figure 2 Mean Plasma Concentration of Naloxone, (a) 0-6 hrs and (b) 0-1 hour Following Intranasal Administration of REXTOVY Nasal Spray (4mg) and IM Injection of Naloxone HCl (0.4mg)

(a)

(b)

The dose-normalized relative bioavailability of one (4 mg) dose of REXTOVY Nasal Spray as compared to the 0.4 mg dose of naloxone hydrochloride administered by IV was 40.7%.

Distribution
Following parenteral administration, naloxone hydrochloride is distributed in the body and readily crosses the placenta. Plasma protein binding occurs but is relatively weak. Plasma albumin is the major binding constituent, but significant binding of naloxone hydrochloride also occurs to plasma constituents other than albumin. It is not known whether naloxone is excreted into human milk.

Elimination
Following a single intranasal administration of REXTOVY Nasal Spray (4 mg dose of naloxone hydrochloride), the mean plasma half-life of naloxone hydrochloride in healthy adults was approximately 67.6 minutes, which was shorter than that observed after administrations of a 0.4 mg naloxone hydrochloride IM injection, where the half-life was 75.7 minutes. The half-life of 2 mg naloxone hydrochloride IV infusion is approximately 66.2 minutes.

Metabolism
Naloxone hydrochloride is metabolized in the liver, primarily by glucuronide conjugation, with naloxone-3-glucuronide as the major metabolite.

Excretion
Naloxone is excreted mainly as metabolites in urine.

13 NONCLINICAL TOXICOLOGY

13.1 Carcinogenesis, Mutagenesis, Impairment of Fertility

Carcinogenesis
Long-term animal studies to evaluate the carcinogenic potential of naloxone have not been completed.

Mutagenesis
Naloxone was weakly positive in the Ames mutagenicity and in the in vitro human lymphocyte chromosome aberration test but was negative in the in vitro Chinese hamster V79 cell HGPRT mutagenicity assay and in the in vivo rat bone marrow chromosome aberration study.

Impairment of Fertility
Reproduction studies conducted in mice and rats at doses 6-times and 12-times, respectively, a human dose of 8 mg/day (two REXTOVY Nasal Sprays) based on body surface area comparison, demonstrated no adverse effects on fertility of naloxone hydrochloride.

16 HOW SUPPLIED/STORAGE AND HANDLING

16.1 How Supplied

Each carton contains two unit-dose REXTOVY Nasal Spray devices. Each device delivers a single spray containing 4 mg of naloxone hydrochloride.

One carton containing two REXTOVY Nasal Spray devices: NDC 76329-3669-2

REXTOVY Nasal Spray is not made with natural rubber latex.

16.2 Storage and Handling

Store REXTOVY Nasal Spray in the blister and cartons provided.

Store at 20°C to 25°C (68°F to 77°F); excursions permitted from 4°C to 40°C (39°F to 104°F). Do not freeze. Protect from light.

Naloxone Hydrochloride freezes at temperatures below -15°C (5°F). If this happens, the device will not spray. If Naloxone Hydrochloride is frozen and is needed in an emergency, do NOT wait for Naloxone Hydrochloride to thaw. Get emergency medical help right away. However, Naloxone Hydrochloride may be thawed by allowing it to sit at room temperature for 15 minutes, and it may still be used if it has been thawed after being previously frozen.

17 PATIENT COUNSELING INFORMATION

Advise the patient and family members or caregivers to read the FDA-approved patient labeling (Patient Information and Instructions for Use).

Recognition of Opioid Overdose
Inform patients and their family members or caregivers about how to recognize the signs and symptoms of an opioid overdose such as the following:

- Extreme somnolence -inability to awaken a patient verbally or upon a firm sternal rub.
- Respiratory depression -this can range from slow or shallow respiration to no respiration in a patient who is unarousable.
- Other signs and symptoms that may accompany somnolence and respiratory depression include the following:

◦Miosis
◦Bradycardia and/or hypotension.

Risk of Recurrent Respiratory and Central Nervous System Depression
Instruct patients and their family members or caregivers that, since the duration of action of most opioids may exceed that of REXTOVY Nasal Spray, they must seek immediate emergency medical assistance after administration of REXTOVY Nasal Spray and keep the patient under continued surveillance [see Dosage and Administration (2.2), Warnings and Precautions (5.3)].

Limited Efficacy for/with Partial Agonists or Mixed Agonist/Antagonists
Instruct patients and their family members or caregivers that the reversal of respiratory depression caused by partial agonists or mixed agonist/antagonists, such as buprenorphine and pentazocine, may be incomplete and may require higher doses of naloxone hydrochloride or repeated administration of REXTOVY Nasal Spray, using a new nasal spray device each time [see Dosage and Administration (2.3), Warnings and Precautions (5.2)].

Precipitation of Severe Opioid Withdrawal
Instruct patients and their family members or caregivers that the use of REXTOVY Nasal Spray in patients who are opioid dependent may precipitate opioid withdrawal [see Warnings and Precautions (5.3), Adverse Reactions (6)].

Administration Instructions
Instruct patients and their family members or caregivers to:

- Ensure REXTOVY Nasal Spray is readily available in locations where persons may be intentionally or accidentally exposed to an opioid overdose (i.e., opioid emergencies).
- Use each REXTOVY Nasal Spray device only one time. Do not test or prime prior to use [see Dosage and Administration (2.1)].
- Administer REXTOVY Nasal Spray as quickly as possible if a patient is unresponsive and an opioid overdose is suspected, even when in doubt, because prolonged respiratory depression may result in damage to the central nervous system or death. REXTOVY Nasal Spray is not a substitute for emergency medical care [see Dosage and Administration (2.1)].
- Lay the patient on their back and administer REXTOVY Nasal Spray into one nostril while providing support to the back of the neck to allow the head to tilt back [see Dosage and Administration (2.1)].
- If the patient responds by waking up to the voice or touch or starts breathing normally, place them in the recovery position by turning them to their side as shown in the Instructions for Use and call for emergency medical assistance immediately after administration of REXTOVY Nasal Spray. Additional supportive and/or resuscitative measures may be helpful while awaiting emergency medical assistance [see Dosage and Administration (2.1)].
- Monitor the patient and re-administer additional doses of REXTOVY Nasal Spray every 2 to 3 minutes, using a new REXTOVY Nasal Spray device. If the patient is not responding or responds and then relapses back into respiratory depression, administer REXTOVY Nasal Spray in alternate nostrils with each dose [see Dosage and Administration (2.1)].
- Replace REXTOVY Nasal Spray before its expiration date.

International Medication Systems, Limited
So. El Monte, CA 91733, U.S.A.
An Amphastar Pharmaceuticals Company
Rev. 06-2023

6936690J

Instructions for Use REXTOVY (rex toe' vee) (Naloxone Hydrochloride) Nasal Spray

You and your family members or caregivers should read the Instructions for Use that comes with REXTOVY™ Nasal Spray before using it. Talk to your healthcare provider if you and your family members or caregivers have any questions about the use of REXTOVY™ Nasal Spray.

Use REXTOVY™ Nasal Spray for known or suspected opioid overdose in adults and children.

Important: For use in the nose only.

- Do not remove or test the REXTOVY™ Nasal Spray until ready to use.
- Each REXTOVY™ Nasal Spray has 1 dose and cannot be reused.
- You do not need to prime REXTOVY™ Nasal Spray.

How to use REXTOVY™ Nasal Spray:

How should I store REXTOVY™ Nasal Spray?

- Store at room temperature between 68°F to 77°F (20°C to 25°C). REXTOVY™ Nasal Spray may be stored for short periods between 39°F to 104°F (4°C to 40°C).
- Do not freeze. Do not expose to temperatures below 39°F (4°C) or above 104°F (40°C).
- Keep REXTOVY™ Nasal Spray in its box until ready to use. Protect from light.
- Replace REXTOVY™ Nasal Spray before the expiration date on the box.

Keep REXTOVY™ Nasal Spray and all medicines out of the reach of children.

Distributed by International Medication Systems, Limited, So. El Monte, CA 91733, U.S.A.
For more information, go to www.amphastar.com or call 1-800-423-4136.

This Instructions for Use has been approved by the U.S. Food and Drug Administration. Issued: 06/2023

7036690F/6-23

PATIENT INFORMATION REXTOVY (rex toe' vee) (Naloxone Hydrochloride) Nasal Spray

You and your family members or caregivers should read this Patient Information leaflet before an opioid emergency happens. This information does not take the place of talking with your healthcare provider about your medical condition or your treatment.

What is the most important information I should know about REXTOVY™ Nasal Spray?

REXTOVY™ Nasal Spray is used to temporarily reverse the effects of opioid medicines. The medicine in REXTOVY™ Nasal Spray has no effect in people who are not taking opioid medicines. Always carry REXTOVY™ Nasal Spray with you in case of an opioid emergency.

1. Use REXTOVY™ Nasal Spray right away if you or your caregiver think signs or symptoms of an opioid emergency are present, even if you are not sure, because an opioid emergency can cause severe injury or death. Signs and symptoms of an opioid emergency may include:

- unusual sleepiness and you are not able to awaken the person with a loud voice or by rubbing firmly on the middle of their chest (sternum)
- breathing problems including slow or shallow breathing in someone difficult to awaken or who looks like they are not breathing
- the black circle in the center of the colored part of the eye (pupil) is very small, sometimes called “pinpoint pupils,” in someone difficult to awaken

2. Family members, caregivers, or other people who may have to use REXTOVY™ Nasal Spray in an opioid emergency should know where REXTOVY™ Nasal Spray is stored and how to give REXTOVY™ Nasal Spray before an opioid emergency happens.

3. Get emergency medical help right away after giving the first dose of REXTOVY™ Nasal Spray. Rescue breathing or CPR (cardiopulmonary resuscitation) may be given while waiting for emergency medical help.

4. The signs and symptoms of an opioid emergency can return after REXTOVY™ Nasal Spray is given. If this happens, give another dose after 2 minutes, then every 2 to 3 minutes using a new REXTOVY™ Nasal Spray and watch the person closely until emergency help is received.

What is REXTOVY™ Nasal Spray?

- REXTOVY™ Nasal Spray is a prescription medicine used in adults and children for the treatment of an opioid emergency such as an overdose or a possible opioid overdose with signs of breathing problems and severe sleepiness or not being able to respond.
- REXTOVY™ Nasal Spray is to be given right away and does not take the place of emergency medical care. Get emergency medical help right away after giving the first dose of REXTOVY™ Nasal Spray, even if the person wakes up.
- REXTOVY™ Nasal Spray is safe and effective in children for known or suspected opioid overdose.

Who should not use REXTOVY™ Nasal Spray?

Do not use REXTOVY™ Nasal Spray if you are allergic to naloxone hydrochloride or any of the ingredients in REXTOVY™ Nasal Spray. See the end of this leaflet for a complete list of ingredients in REXTOVY™ Nasal Spray.

What should I tell my healthcare provider before using REXTOVY™ Nasal Spray?

Before using REXTOVY™ Nasal Spray, tell your healthcare provider about all of your medical conditions, including if you:

- have heart problems
- are pregnant or plan to become pregnant. Use of REXTOVY™ Nasal Spray may cause withdrawal symptoms in your unborn baby. Your unborn baby should be examined by a healthcare provider right away after you use REXTOVY™ Nasal Spray.
- are breastfeeding or plan to breastfeed. It is not known if REXTOVY™ Nasal Spray passes into your breast milk.

Tell your healthcare provider about the medicines you take, including prescription and over-the-counter medicines, vitamins, and herbal supplements.

How should I use REXTOVY™ Nasal Spray?
Read the "Instructions for Use" at the end of this Patient Information leaflet for detailed information about the right way to use REXTOVY™ Nasal Spray.

- Use REXTOVY™ Nasal Spray exactly as prescribed by your healthcare provider.
- Each REXTOVY™ Nasal Spray contains only 1 dose of medicine and cannot be reused.
- Lay the person on their back. Support their neck with your hand and allow the head to tilt back before giving REXTOVY™ Nasal Spray.
- REXTOVY™ Nasal Spray should be given into one nostril.
- Call for emergency medical assistance immediately after the first dose of REXTOVY™ Nasal Spray.
- If the person responds by waking up to the voice or touch or starts breathing normally, place the person on their side (recovery position).
- If the person does not respond or stops breathing normally and additional doses are needed, give REXTOVY™ Nasal Spray in the other nostril.

What are the possible side effects of REXTOVY™ Nasal Spray?
REXTOVY™ Nasal Spray may cause serious side effects, including:

- Sudden opioid withdrawal symptoms. In someone who has been using opioids regularly, opioid withdrawal symptoms can happen suddenly after receiving REXTOVY™ Nasal Spray and may include

o body aches

o sneezing

o nervousness

o diarrhea

o goose bumps

o restlessness or irritability

o increased heart rate

o sweating

o shivering or trembling

o fever

o yawning

o stomach cramping

o runny nose

o nausea or vomiting

o weakness

o increased blood pressure

In infants under 4 weeks old who have been receiving opioids regularly, sudden opioid withdrawal may be life-threatening if not treated the right way. Signs and symptoms include: seizures, crying more than usual, and increased reflexes.

The most common side effects of REXTOVY™ Nasal Spray include tingling in your mouth, and headache.
These are not all of the possible side effects of REXTOVY™ Nasal Spray. Call your doctor for medical advice about side effects. You may report side effects to FDA at 1-800-FDA-1088.

How should I store REXTOVY™ Nasal Spray?

- Store at room temperature between 68°F to 77°F (20°C to 25°C). REXTOVY™ Nasal Spray may be stored for short periods between 39°F to 104°F (4°C to 40°C).
- Do not freeze. Do not expose to temperatures below 39°F (4°C) or above 104°F (40°C).
- Keep REXTOVY™ Nasal Spray in its box until ready to use. Protect from light.
- Replace REXTOVY™ Nasal Spray before the expiration date on the box.

Keep REXTOVY™ Nasal Spray and all medicines out of the reach of children.

General information about the safe and effective use of REXTOVY™ Nasal Spray.
Medicines are sometimes prescribed for purposes other than those listed in a Patient Information leaflet. Do not use REXTOVY™ Nasal Spray for a condition for which it was not prescribed. You can ask your pharmacist or healthcare provider for information about REXTOVY™ Nasal Spray that is written for health professionals.

What are the ingredients in REXTOVY™ Nasal Spray?
Active ingredient: naloxone hydrochloride
Inactive ingredients: sodium chloride, sodium hydroxide to adjust pH and water for injection USP
REXTOVY™ Nasal Spray is not made with natural rubber latex.

Distributed by International Medication Systems, Limited, So. El Monte, CA 91733, U.S.A.
For more information, go to www.amphastar.com or call 1-800-423-4136.

This Patient Information has been approved by the U.S. Food and Drug Administration. Issued: 06/2023

Carton Label

Principal Display Panel Text:

NDC 76329-3669-2 Rx Only

REXTOVY™
(Naloxone HCl)
Nasal Spray

4 mg per Device
For use in the Nose Only

USE FOR KNOWN OR SUSPECTED
OPIOID OVERDOSE
Seek Emergency Medical Attention

See Instructions for Use for
Administration.
This box contains two (2) unit-dose
4 mg NASAL Spray devices.

Deliver full dose into one nostril

Store at 20˚C to 25˚C (68˚F to 77˚F);
excursions permitted from 4˚C to 40˚C
(39˚F to 104˚F).

- Do not freeze
- Protect from excessive heat
- Protect from light

INTERNATIONAL MEDICATION SYSTEMS, LIMITED
So. El Monte, CA 91733, U.S.A.
An Amphastar Pharmaceuticals Company
www.Amphastar.com
5636690D/3-23 Stock No. 3669